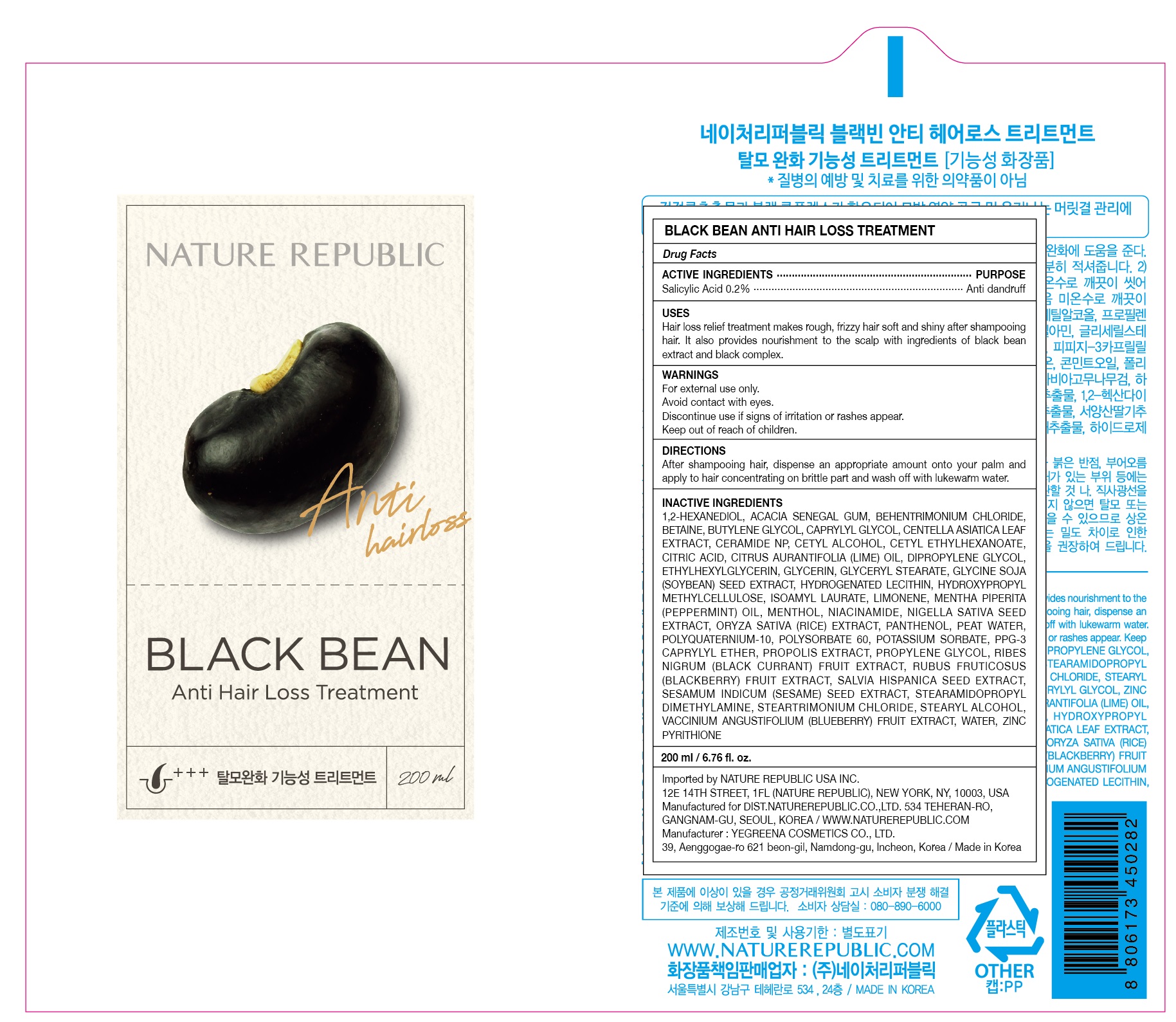 DRUG LABEL: BLACK BEAN ANTI HAIR LOSS TREATMENT
NDC: 51346-515 | Form: SHAMPOO
Manufacturer: NATURE REPUBLIC CO., LTD.
Category: otc | Type: HUMAN OTC DRUG LABEL
Date: 20201029

ACTIVE INGREDIENTS: Salicylic Acid 0.4 g/200 mL
INACTIVE INGREDIENTS: 1,2-Hexanediol; ACACIA

ACTIVE INGREDIENT

Salicylic Acid 0.2%

INACTIVE INGREDIENTS

1,2-Hexanediol, Acacia Senegal Gum, Behentrimonium Chloride, Betaine, Butylene Glycol, Caprylyl Glycol, Centella Asiatica Leaf Extract, Ceramide NP, Cetyl Alcohol, Cetyl Ethylhexanoate, Citric Acid, Citrus Aurantifolia (Lime) Oil, Dipropylene Glycol, Ethylhexylglycerin, Glycerin, Glyceryl Stearate, Glycine Soja (Soybean) Seed Extract, Hydrogenated Lecithin, Hydroxypropyl Methylcellulose, Isoamyl Laurate, Limonene, Mentha Piperita (Peppermint) Oil, Menthol, Niacinamide, Nigella Sativa Seed Extract, Oryza Sativa (Rice) Extract, Panthenol, Peat water, Polyquaternium-10, Polysorbate 60, Potassium Sorbate, PPG-3 Caprylyl Ether, Propolis Extract, Propylene Glycol, Ribes Nigrum (Black Currant) Fruit Extract, Rubus Fruticosus (Blackberry) Fruit Extract, Salvia Hispanica Seed Extract, Sesamum Indicum (Sesame) Seed Extract, Stearamidopropyl Dimethylamine, Steartrimonium Chloride, Stearyl Alcohol, Vaccinium Angustifolium (Blueberry) Fruit Extract, Water, Zinc Pyrithione

PURPOSE

Anti dandruff

WARNINGS

For external use only.
Avoid contact with eyes.
Discontinue use if signs of irritation or rashes appear.
Keep out of reach of children.

KEEP OUT OF REACH OF CHILDREN

Uses

Hair loss relief treatment makes rough, frizzy hair soft and shiny after shampooing hair. It also provides nourishment to the scalp with ingredients of black bean extract and black complex.

Directions

After shampooing hair, dispense an appropriate amount onto your palm and apply to hair concentrating on brittle part and wash off with lukewarm water.